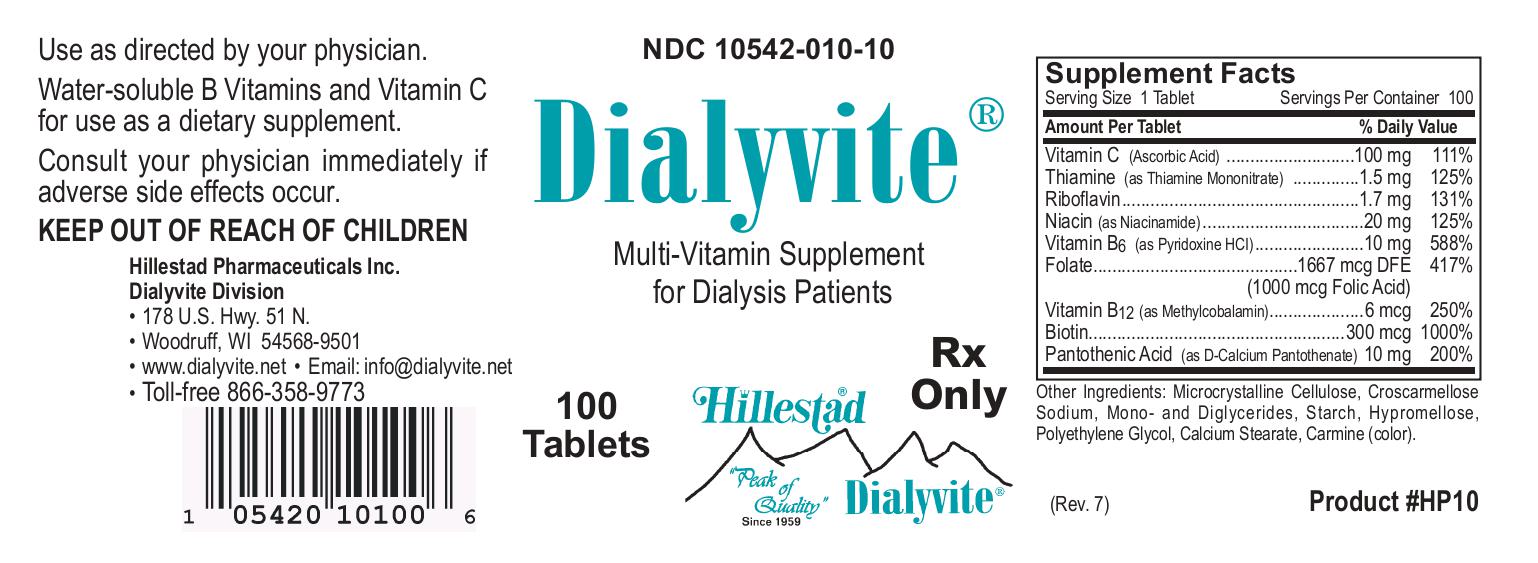 DRUG LABEL: Dialyvite
NDC: 10542-010 | Form: TABLET, COATED
Manufacturer: Hillestad Pharmaceuticals USA
Category: prescription | Type: HUMAN PRESCRIPTION DRUG LABEL
Date: 20260127

ACTIVE INGREDIENTS: Ascorbic Acid 100 mg/1 1; Thiamine Mononitrate 1.5 mg/1 1; Riboflavin 1.7 mg/1 1; Niacinamide 20 mg/1 1; Pyridoxine Hydrochloride 10 mg/1 1; Folic Acid 1 mg/1 1; Cobalamin 6 ug/1 1; Biotin 300 ug/1 1; Calcium Pantothenate 10 mg/1 1
INACTIVE INGREDIENTS: Microcrystalline Cellulose; Croscarmellose Sodium; Glyceryl Monostearate; Starch, Corn; Hypromellose, unspecified; Polyethylene Glycol, unspecified; Calcium Stearate; Cochineal

Dialyvite

DESCRIPTION

Dialyvite is a prescription folic acid supplement with additional nutrients for kidney dialysis patients. Dialyvite is a small, round, light pink, clear-coated tablet, with debossed "H" on one side.

Each tablet contains:

Folic Acid.....1 mg

Vitamin C (Ascorbic Acid).....100 mg

Thiamine (Thiamine Mononitrate).....1.5 mg

Riboflavin.....1.7 mg

Niacinamide.....20 mg

Vitamin B6 (Pyridoxine HCl).....10 mg

Vitamin B12 (Methylcobalamin).....6 mcg

Biotin.....300 mcg

Pantothenic Acid (Calcium Pantothenate).....10 mg

Inactive ingredients:

Microcrystalline Cellulose, Croscarmellose Sodium, Mono- and Diglycerides, Starch, Hypromellose, Polyethylene Glycol, Calcium Stearate, Carmine (color).

INDICATIONS AND USAGE

Dialyvite is a prescription folic acid supplement with additional nutrients indicated for use in improving the nutritional status of renal dialysis patients.

CONTRAINDICATIONS

This product is contraindicated in patients with known hypersensitivity to any of the ingredients.

PRECAUTIONS

Folic acid supplementation may obscure pernicious anemia, in that hematologic remission can occur while neurological manifestations progress.

Keep out of reach of children.

ADVERSE REACTIONS

Allergic sensitizations have been reported following oral administration of folic acid.

Consult your physician immediately if adverse side effects occur.

DOSAGE AND ADMINISTRATION

Take one tablet per day or as directed by your physician, orally.

PRINCIPAL DISPLAY PANEL

NDC 10542-010-10

Dialyvite

Multivitamin Supplement for Dialysis Patients

100 Tablets